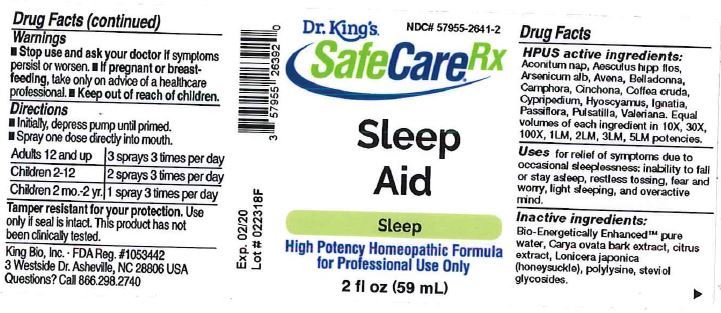 DRUG LABEL: Sleep Aid
NDC: 57955-2641 | Form: LIQUID
Manufacturer: King Bio Inc.
Category: homeopathic | Type: HUMAN OTC DRUG LABEL
Date: 20180424

ACTIVE INGREDIENTS: ACONITUM NAPELLUS 59 [hp_X]/59 mL; AESCULUS HIPPOCASTANUM FLOWER 59 [hp_X]/59 mL; ARSENIC TRIOXIDE 59 [hp_X]/59 mL; AVENA SATIVA FLOWERING TOP 59 [hp_X]/59 mL; ATROPA BELLADONNA 59 [hp_X]/59 mL; CAMPHOR (NATURAL) 59 [hp_X]/59 mL; CINCHONA OFFICINALIS BARK 59 [hp_X]/59 mL; ARABICA COFFEE BEAN 59 [hp_X]/59 mL; CYPRIPEDIUM PARVIFOLUM ROOT 59 [hp_X]/59 mL; HYOSCYAMUS NIGER 59 [hp_X]/59 mL; STRYCHNOS IGNATII SEED 59 [hp_X]/59 mL; PASSIFLORA INCARNATA FLOWERING TOP 59 [hp_X]/59 mL; PULSATILLA VULGARIS 59 [hp_X]/59 mL; VALERIAN 59 [hp_X]/59 mL
INACTIVE INGREDIENTS: WATER; CARYA OVATA BARK; CITRUS BIOFLAVONOIDS; LONICERA JAPONICA FLOWER; POLYEPSILON-LYSINE (4000 MW); REBAUDIOSIDE A

Sleep Aid™

ACTIVE INGREDIENT

Drug Facts__________________________________________________________________________________________________________

HPUS active ingredients: Aconitum nap, Aesculus hipp, flos, Arsenicum alb, Avena, Belladonna, Camphora, Cinchona, Coffea cruda, Cypripedium, Hyoscyamus, Ignatia, Passiflora, Pulsatilla, Valerian.

Equal volumes of each ingredient in 10X, 30X, 100X, 1LM, 2LM, 3LM, 5LM potencies.

INDICATIONS AND USAGE

Uses for relief of symptoms due to occasional sleeplessness: inability to fall or stay asleep, restless tossing, fear and worry, light sleeping, and overactive mind.

INACTIVE INGREDIENT

Inactive Ingredients: Bio-Energetically Enhanced™ pure water, Carya ovaa bark exract, citrus extract, Lonicera japonica (honeysuckle), polylysine, steviol glycosides.

Warnings

- Stop use and ask your doctor if symptoms persist or worsen.
- If pregnant or breast-feeding, take only on advice of a healthcare professional.

- Keep out of reach of children.

Directions

- Initially, depress pump until primed.
- Spray one dose directly into mouth.
- Adults 12 and up: 3 sprays 3 times per day.
- Children 2-12: 2 sprays 3 times per day.
- Children 2 mo.-2yr: 1 spray 3 times per day.

OTHER SAFETY INFORMATION

Tamper resistant for your protection. Use only if safety seal is intact. This product has not been clinically tested.

PURPOSE

Uses for relief of symptoms due to occasional sleeplessness:

- inability to fall or stay asleep
- restless tossing
- fear and worry
- light sleeping
- overactive mind